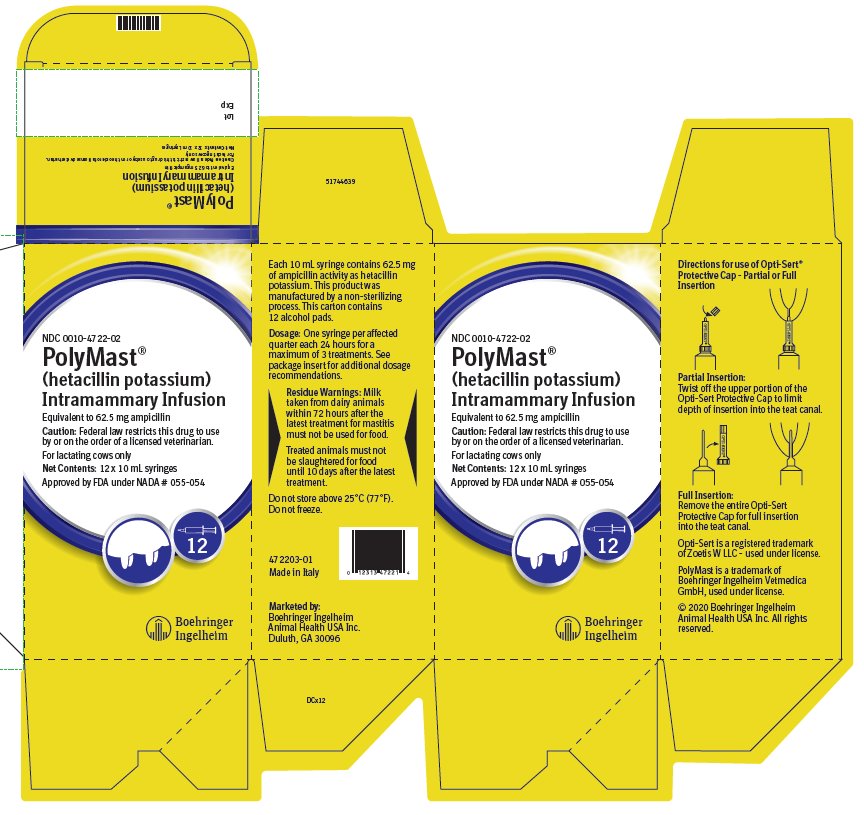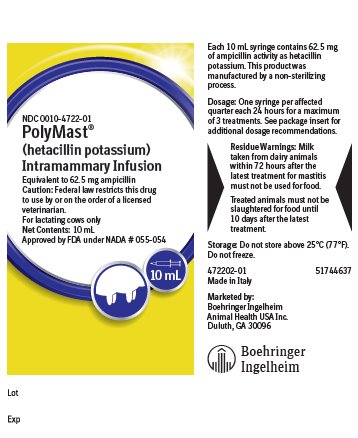 DRUG LABEL: PolyMast
NDC: 0010-4722 | Form: GEL
Manufacturer: Boehringer Ingelheim Animal Health USA Inc.
Category: animal | Type: PRESCRIPTION ANIMAL DRUG LABEL
Date: 20211011

ACTIVE INGREDIENTS: HETACILLIN POTASSIUM 62.5 mg/10 mL
INACTIVE INGREDIENTS: PEANUT OIL; HYDROGENATED CASTOR OIL

PolyMast® (hetacillin potassium)
Intramammary Infusion
For lactating cows only

Approved by FDA under NADA # 055-054

Caution:

Federal law restricts this drug to use by or on the order of a licensed veterinarian.

Description:

POLYMAST (hetacillin potassium) is a broad-spectrum agent which provides bactericidal activity against a wide range of common gram-positive and gram-negative bacteria. It is derived from 6-aminopenicillanic acid and is chemically related to ampicillin.

Each 10 mL disposable syringe contains hetacillin potassium equivalent to 62.5 mg ampicillin activity in a stable peanut oil gel. This product was manufactured by a non-sterilizing process.

Action:

Hetacillin provides bactericidal levels of the active antibiotic, ampicillin. In vitro studies have demonstrated susceptibility of the following organisms to ampicillin: Streptococcus agalactiae, Streptococcus dysgalactiae, Staphylococcus aureus and Escherichia coli.

Indications:

For the treatment of acute, chronic or subclinical bovine mastitis. POLYMAST should be used at the first signs of inflammation or at the first indication of any alteration in the milk. Subclinical infections should be treated immediately upon determining, by C.M.T. or other tests, that the leukocyte count is elevated, or that a susceptible pathogen has been cultured from the milk.

POLYMAST has been shown to be efficacious in the treatment of mastitis in lactating cows caused by susceptible strains of Streptococcus agalactiae, Streptococcus dysgalactiae, Staphylococcus aureus and Escherichia coli.

Polycillin® (ampicillin) Susceptibility Test Discs, 10 mcg, should be used to estimate the in vitro susceptibility of bacteria to hetacillin.

Dosage and Administration:

Infuse the entire contents of one syringe (10 mL) into each infected quarter. Repeat at 24-hour intervals until a maximum of three treatments has been given.

If definite improvement is not noted within 48 hours after treatment, the causal organism should be further investigated.

Wash the udder and teats thoroughly with warm water containing a suitable dairy antiseptic and dry, preferably using individual paper towels. Carefully scrub the teat end and orifice with 70% alcohol, using a separate swab for each teat. Allow to dry.

POLYMAST is packaged with the Opti-Sert® Protective Cap.

For partial insertion: Twist off upper portion of the Opti-Sert Protective Cap to expose 3–4 mm of the syringe tip.

For full insertion: Remove protective cap to expose the full length of the syringe tip.

Insert syringe tip into the teat canal and expel the entire contents of one syringe into each infected quarter. Withdraw the syringe and gently massage the quarter to distribute the medication.

Do not infuse contents of the mastitis syringe into the teat canal if the Opti-Sert Protective Cap is broken or damaged.

Residue Warnings:

Milk that has been taken from animals during treatment and for 72 hours (6 milkings) after the latest treatment must not be used for food. Treated animals must not be slaughtered for food until 10 days after the latest treatment.

Precautions

Because it is a derivative of 6-aminopenicillanic acid, POLYMAST has the potential for producing allergic reactions. Such reactions are rare; however, should they occur, treatment should be discontinued and the subject treated with antihistamines, pressor amines, such as epinephrine or corticosteroids.

The drug does not resist destruction by penicillinase and, hence, is not effective against strains of staphylococcus resistant to penicillin G.

Storage:

Do not store above 25°C (77°F). Do not freeze.

How Supplied:

POLYMAST is supplied as 10 mL syringes containing 62.5 mg ampicillin activity per syringe. One display carton contains 12 syringes. One pail contains 144 syringes.

NDC 0010-4722-01 - 10 mL syringe; NDC 0010-4722-02 -12 syringes; NDC 0010-4722-03 - 144 syringes.

Opti-Sert is a registered trademark of Zoetis W LLC - used under license.

POLYMAST is a trademark of Boehringer Ingelheim Vetmedica GmbH, used under license.

© 2020 Boehringer Ingelheim Animal Health USA Inc. All rights reserved.

Made in Italy

472201-01 51744638

Marketed by:

Boehringer Ingelheim Animal Health USA Inc.

Duluth, GA 30096

Principal Display Panel – 12 x 10 mL syringe display carton

NDC 0010-0010-4722-02

PolyMast®

(hetacillin potassium)

Intramammary Infusion

Equivalent to 62.5 mg ampicillin

Caution: Federal law restricts this drug to use by on on the order of a licensed veterinarian.

For lacating cows only

Net Contents: 12 x 10 mL syringes

Approved by FDA under NADA # 055-054